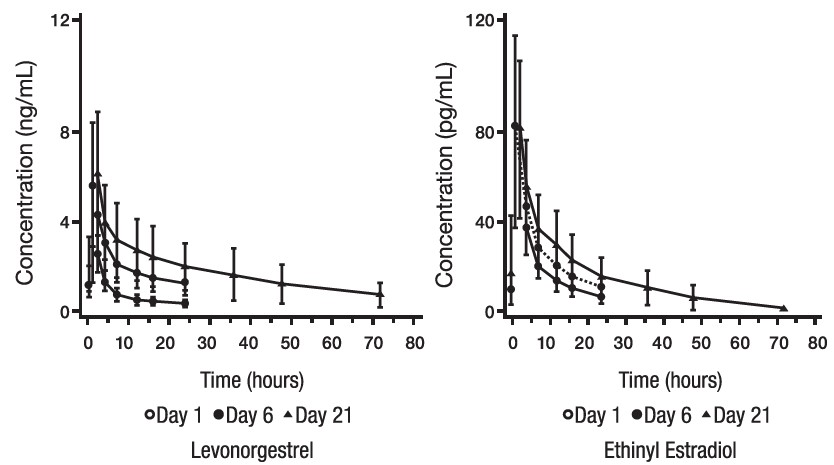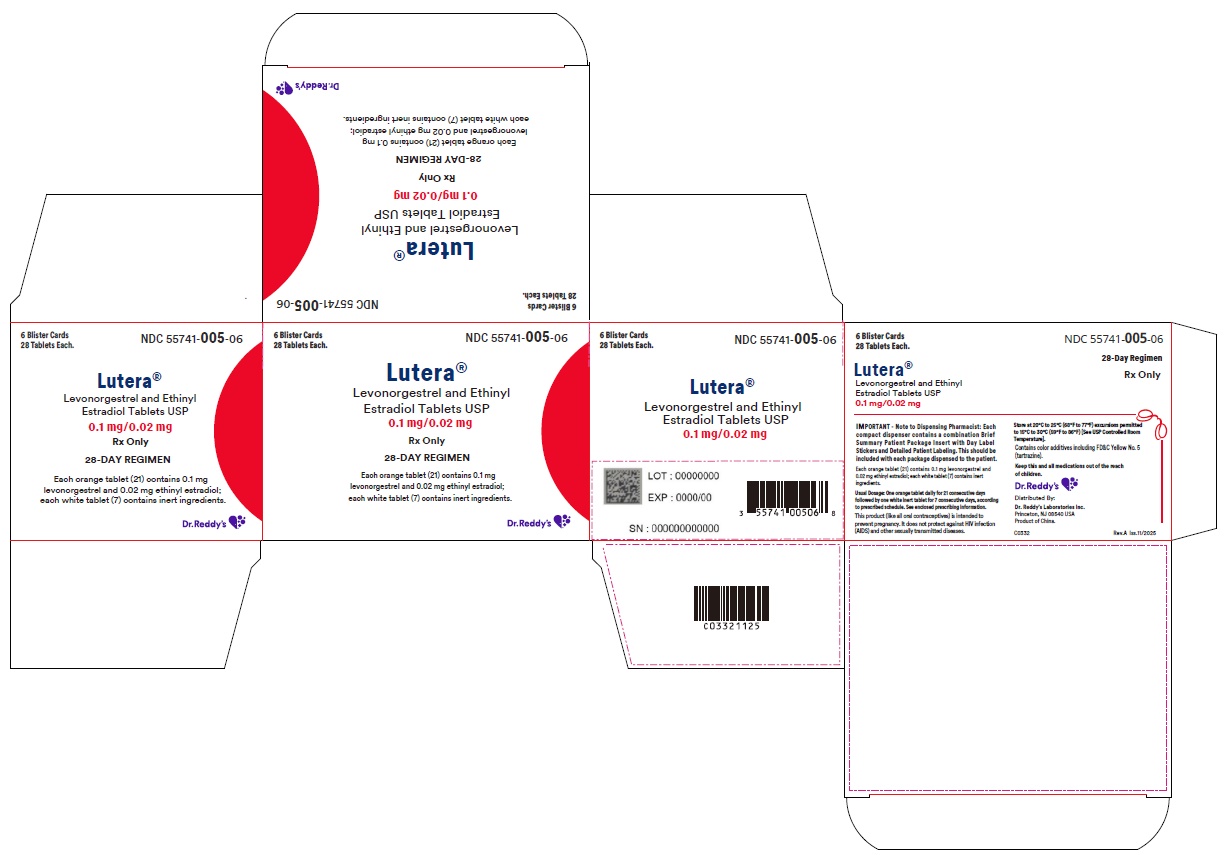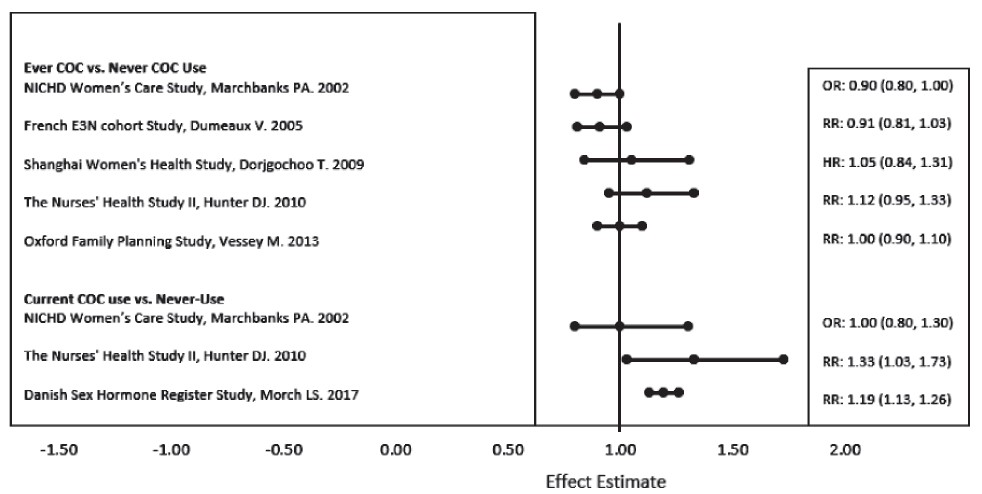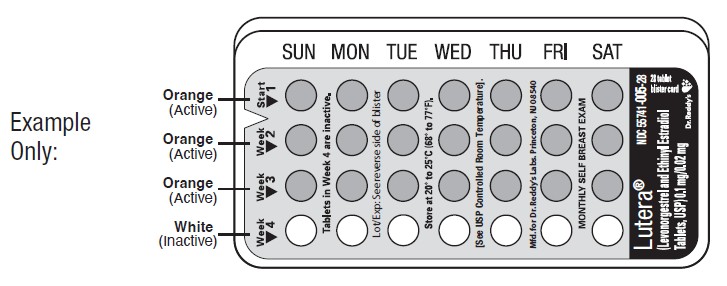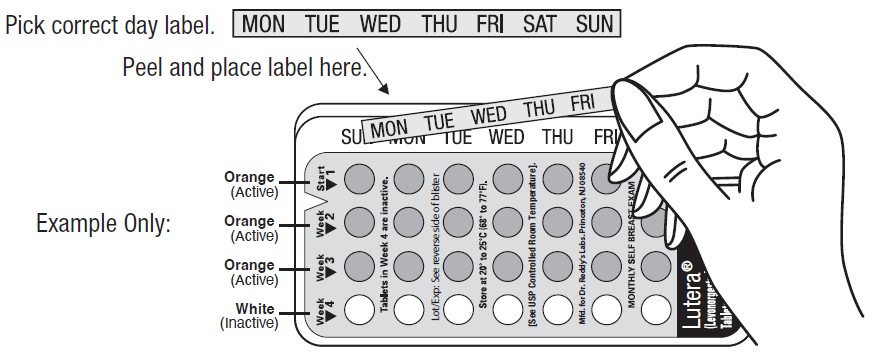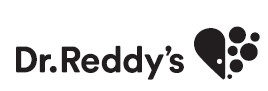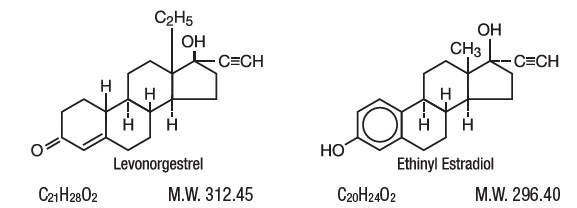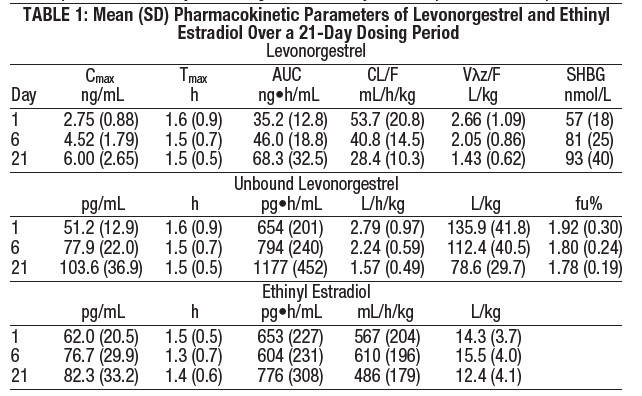 DRUG LABEL: Lutera
NDC: 55741-005 | Form: KIT | Route: ORAL
Manufacturer: Dr. Reddy’s Laboratories Inc.
Category: prescription | Type: HUMAN PRESCRIPTION DRUG LABEL
Date: 20260213

ACTIVE INGREDIENTS: LEVONORGESTREL 0.1 mg/1 1; ETHINYL ESTRADIOL 0.02 mg/1 1
INACTIVE INGREDIENTS: FD&C YELLOW NO. 5; FD&C YELLOW NO. 6; FD&C RED NO. 40; TITANIUM DIOXIDE; POLYVINYL ALCOHOL; TALC; POLYETHYLENE GLYCOL 3350; LECITHIN, SOYBEAN; FERROSOFERRIC OXIDE; TITANIUM DIOXIDE; POLYDEXTROSE; HYPROMELLOSES; TRIACETIN; POLYETHYLENE GLYCOL 8000; LACTOSE MONOHYDRATE; MAGNESIUM STEARATE; STARCH, CORN

Rx only

Patients should be counseled that oral contraceptives do not protect against transmission of HIV (AIDS) and other sexually transmitted diseases (STDs) such as chlamydia, genital herpes, genital warts (human papillomavirus) gonorrhea, hepatitis B, and syphilis.

DESCRIPTION

21 orange active tablets each containing 0.10 mg of levonorgestrel, d(-)-13β-ethyl-17α-ethinyl-17β-hydroxygon-4-en-3-one, a totally synthetic progestogen, and 0.02 mg of ethinyl estradiol, 17α-ethinyl-1,3,5(10)-estratriene-3,17β-diol. The inactive ingredients present are FD&C Yellow #5 Aluminum Lake, FD&C Yellow #6 Aluminum Lake, FD&C Red #40 Aluminum Lake, titanium dioxide, polyvinyl alchol, talc, macrogol/polyethylene glycol 3350 NF, lecithin (soya), iron oxide black, lactose monohydrate, magnesium stearate and pregelatinized corn starch.

7 white tablets, each containing the following inactive ingredients: titanium dioxide, polydextrose, hypromellose, triacetin, macrogol/polyethylene glycol 8000, lactose monohydrate, magnesium stearate and pregelatinized corn starch.

CLINICAL PHARMACOLOGY

Mode of Action

Combination oral contraceptives prevent pregnancy primarily by suppressing ovulation.

Pharmacokinetics

Absorption

No specific investigation of the absolute bioavailability of Lutera (Levonorgestrel and Ethinyl Estradiol Tablets, USP) in humans has been conducted. However, literature indicates that levonorgestrel is rapidly and completely absorbed after oral administration (bioavailability about 100%) and is not subject to first-pass metabolism. Ethinyl estradiol is rapidly and almost completely absorbed from the gastrointestinal tract but, due to first-pass metabolism in gut mucosa and liver, the bioavailability of ethinyl estradiol is between 38% and 48%.

After a single dose of levonorgestrel and ethinyl estradiol tablets to 22 women under fasting conditions, maximum serum concentrations of levonorgestrel are 2.8 ± 0.9 ng/mL (mean ± SD) at 1.6 ± 0.9 hours. At steady state, attained from day 19 onwards, maximum levonorgestrel concentrations of 6.0 ± 2.7 ng/mL are reached at 1.5 ± 0.5 hours after the daily dose. The minimum serum levels of levonorgestrel at steady state are 1.9 ± 1.0 ng/mL. Observed levonorgestrel concentrations increased from day 1 (single dose) to days 6 and 21 (multiple doses) by 34% and 96%, respectively (Figure 1).

Unbound levonorgestrel concentrations increased from day 1 to days 6 and 21 by 25% and 83%, respectively. The kinetics of total levonorgestrel are non-linear due to an increase in binding of levonorgestrel to sex hormone binding globulin (SHBG), which is attributed to increased SHBG levels that are induced by the daily administration of ethinyl estradiol.

Following a single dose, maximum serum concentrations of ethinyl estradiol of 62 ± 21 pg/mL are reached at 1.5 ± 0.5 hours. At steady state, attained from at least day 6 onwards, maximum concentrations of ethinyl estradiol were 77 ± 30 pg/mL and were reached at 1.3 ± 0.7 hours after the daily dose. The minimum serum levels of ethinyl estradiol at steady state are 10.5 ± 5.1 pg/mL. Ethinyl estradiol concentrations did not increase from days 1 to 6, but did increase by 19% from days 1 to 21 (Figure 1).

FIGURE 1 Mean (SE) levonorgestrel and ethinyl estradiol serum concentrations in 22 subjects receiving 100 mcg levonorgestrel and 20 mcg ethinyl estradiol

TABLE 1 provides a summary of levonorgestrel and ethinyl estradiol pharmacokinetic parameters.

Distribution

Levonorgestrel in serum is primarily bound to SHBG. Ethinyl estradiol is about 97% bound to plasma albumin. Ethinyl estradiol does not bind to SHBG, but induces SHBG synthesis.

Metabolism

Levonorgestrel: The most important metabolic pathway occurs in the reduction of the Δ4-3-oxo group and hydroxylation at positions 2α, 1β, and 16β, followed by conjugation. Most of the metabolites that circulate in the blood are sulfates of 3α, 5β-tetrahydro-levonorgestrel, while excretion occurs predominantly in the form of glucuronides. Some of the parent levonorgestrel also circulates as 17β-sulfate. Metabolic clearance rates may differ among individuals by several-fold, and this may account in part for the wide variation observed in levonorgestrel concentrations among users.

Ethinyl estradiol: Cytochrome P450 enzymes (CYP3A4) in the liver are responsible for the 2-hydroxylation that is the major oxidative reaction. The 2-hydroxy metabolite is further transformed by methylation and glucuronidation prior to urinary and fecal excretion. Levels of Cytochrome P450 (CYP3A) vary widely among individuals and can explain the variation in rates of ethinyl estradiol 2-hydroxylation. Ethinyl estradiol is excreted in the urine and feces as glucuronide and sulfate conjugates, and undergoes enterohepatic circulation.

Excretion

The elimination half-life for levonorgestrel is approximately 36 ± 13 hours at steady state. Levonorgestrel and its metabolites are primarily excreted in the urine (40% to 68%) and about 16% to 48% are excreted in feces. The elimination half-life of ethinyl estradiol is 18 ± 4.7 hours at steady state.

Special Populations

Race

Based on the pharmacokinetic study with levonorgestrel and ethinyl estradiol tablets, there are no apparent differences in pharmacokinetic parameters among women of different races.

Hepatic insufficiency

No formal studies have evaluated the effect of hepatic disease on the disposition of Lutera (levonorgestrel and ethinyl estradiol tablets USP). However, steroid hormones may be poorly metabolized in patients with impaired liver function.

Renal insufficiency

No formal studies have evaluated the effect of renal disease on the disposition of Lutera.

Drug-drug interactions

See PRECAUTIONS - Drug Interactions

INDICATIONS AND USAGE

Lutera is indicated for use by females of reproductive potential to prevent pregnancy.

Limitations of use: The efficacy of Lutera in women with a body mass index (BMI) of > 35 kg/m^2 has not been adequately evaluated.

In a clinical trial with levonorgestrel and ethinyl estradiol tablets, 1,477 subjects had 7,720 cycles of use and a total of 5 pregnancies were reported. This represents an overall pregnancy rate of 0.84 per 100 woman-years. This rate includes patients who did not take the drug correctly. One or more pills were missed during 1,479 (18.8%) of the 7,870 cycles; thus all tablets were taken during 6,391 (81.2%) of the 7,870 cycles. Of the total 7,870 cycles, a total of 150 cycles were excluded from the calculation of the Pearl index due to the use of backup contraception and/or missing 3 or more consecutive pills.

The mean BMI of the study population was 24 kg/m^2. Females with a BMI greater than 30 kg/m^2 accounted for 12.1% (n=179) of the study population. Females with a BMI over 35 kg/m^2 accounted for 4.3% (n=63) of the study population.

CONTRAINDICATIONS

Combination oral contraceptives should not be used in women with any of the following conditions:

Thrombophlebitis or thromboembolic disorders

A history of deep-vein thrombophlebitis or thromboembolic disorders

Cerebrovascular or coronary artery disease (current or past history)

Valvular heart disease with thrombogenic complications

Thrombogenic rhythm disorders

Hereditary or acquired thrombophilias

Prolonged immobilization (especially with major surgery)

Diabetes with vascular involvement

Headaches with focal neurological symptoms or migraine with aura

Women with migraine who are 35 years or older

Uncontrolled hypertension

Known or suspected carcinoma of the breast or personal history of breast cancer

Known or suspected estrogen-or progesterone sensitive malignancy

Undiagnosed abnormal vaginal bleeding

Cholestatic jaundice of pregnancy or jaundice with prior pill use

Hepatic adenomas or carcinomas, or active liver disease

Women who are receiving Hepatitis C drug combinations containing ombitasvir/paritaprevir/ritonavir, with or without dasabuvir, due to the potential for alanine aminotransferase (ALT) elevations (see WARNINGS, RISK OF LIVER ENZYME ELEVATIONS WITH CONCOMITANT HEPATITIS C TREATMENT).

WARNINGS

WARNING: CIGARETTE SMOKING AND SERIOUS CARDIOVASCULAR EVENTS

Cigarette smoking increases the risk of serious cardiovascular events from combined oral contraceptives (COC) use. This risk increases with age, particularly in women over 35 years of age, and with the number of cigarettes smoked. For this reason, COCs, including Lutera, are contraindicated in women who are over 35 years of age and smoke.

The use of oral contraceptives is associated with increased risks of several serious conditions including venous and arterial thrombotic and thromboembolic events (such as myocardial infarction, thromboembolism, and stroke), hepatic neoplasia, gallbladder disease, and hypertension, although the risk of serious morbidity or mortality is very small in healthy women without underlying risk factors. The risk of morbidity and mortality increases significantly in the presence of other underlying risk factors such as certain inherited or acquired thrombophilias, hypertension, hyperlipidemias, obesity, diabetes, and surgery or trauma with increased risk of thrombosis (see CONTRAINDICATIONS).

Practitioners prescribing oral contraceptives should be familiar with the following information relating to these risks.

The information contained in this package insert is principally based on studies carried out in patients who used oral contraceptives with higher doses of estrogens and progestogens than those in common use today. The effect of long-term use of the oral contraceptives with lower doses of both estrogens and progestogens remains to be determined.

Throughout this labeling, epidemiological studies reported are of two types: retrospective or case control studies and prospective or cohort studies. Case control studies provide a measure of the relative risk of disease, namely, a ratio of the incidence of a disease among oral-contraceptive users to that among nonusers. The relative risk does not provide information on the actual clinical occurrence of a disease. Cohort studies provide a measure of attributable risk, which is the difference in the incidence of disease between oral-contraceptive users and nonusers. The attributable risk does provide information about the actual occurrence of a disease in the population. For further information, the reader is referred to a text on epidemiological methods.

1. Thromboembolic Disorders and Other Vascular Problems

Cardiovascular and Cerebrovascular Events

Use of CHCs increases the risk of cardiovascular events and cerebrovascular events, such as myocardial infarction and stroke. The risk of these events with CHC use is greater in females with concomitant risk factors: age 35 years and older, smoking, hypertension, dyslipidemia, diabetes, or obesity. The risk increases with increasing age and with increasing number of cigarettes smoked.

Venous Thromboembolism

Use of CHCs also increases the risk of VTE, such as deep vein thrombosis and pulmonary embolism. The rate of VTE in females using COCs has been estimated to be 3 to 9 cases per 10,000 woman-years. The VTE risk should be considered in the context of relevant subpopulations of females of reproductive potential who are not taking CHCs (ADVERSE REACTIONS).
Risk factors for VTE with CHC use include smoking, obesity, family history of VTE, and prolonged immobilization, in addition to other factors that contraindicate use of CHCs (see CONTRAINDICATIONS). The presence of multiple risk factors for VTE with CHC use may further increase the risk. The risk of VTE is highest during the first year of CHC use and when restarting hormonal contraception after a break of four weeks or longer. The risk of VTE returns to baseline approximately 3 months after CHC use is discontinued.

Postpartum Venous Thromboembolism

The risk of VTE is increased during the first six weeks postpartum. The risk is highest up to four weeks postpartum but remains higher than baseline until at least six weeks postpartum. The presence of multiple risk factors for VTE may further increase the risk. Obstetric complications may extend the elevated risk up to 12 weeks postpartum.

2. Malignant Neoplasms

Breast Cancer

Lutera is contraindicated in females who currently have or have had breast cancer because breast cancer may be hormonally sensitive (see CONTRAINDICATIONS). Epidemiology studies have not found a consistent association between use of combined oral contraceptives (COCs) and breast cancer risk. Studies do not show an association between ever (current or past) use of COCs and risk of breast cancer. However, some studies report a small increase in the risk of breast cancer among current or recent users (<6 months since last use) and current users with longer duration of COC use (see ADVERSE REACTIONS).

Cervical Cancer

Some studies suggest that oral contraceptive use has been associated with an increase in the risk of cervical intraepithelial neoplasia or invasive cervical cancer in some populations of women. However, there continues to be controversy about the extent to which such findings may be due to differences in sexual behavior and other factors.

3. Hepatic Neoplasia

Benign hepatic adenomas are associated with oral-contraceptive use, although the incidence of these benign tumors is rare in the United States. Indirect calculations have estimated the attributable risk to be in the range of 3.3 cases/100,000 for users, a risk that increases after four or more years of use. Rupture of rare, benign, hepatic adenomas may cause death through intra-abdominal hemorrhage.

Studies from Britain have shown an increased risk of developing hepatocellular carcinoma in long-term (>8 years) oral-contraceptive users. However, these cancers are extremely rare in the U.S. and the attributable risk (the excess incidence) of liver cancers in oral-contraceptive users approaches less than one per million users.

4. Risk of Liver Enzyme Elevations with Concomitant Hepatitis C Treatment

During clinical trials with the Hepatitis C combination drug regimen that contains ombitasvir/paritaprevir/ritonavir, with or without dasabuvir, ALT elevations greater than 5 times the upper limit of normal (ULN), including some cases greater than 20 times the ULN, were significantly more frequent in women using ethinyl estradiol-containing medications such as COCs. Discontinue Lutera prior to starting therapy with the combination drug regimen ombitasvir/paritaprevir/ritonavir, with or without dasabuvir (see CONTRAINDICATIONS). Lutera can be restarted approximately 2 weeks following completion of treatment with the combination drug regimen.

5. Ocular Lesions

There have been clinical case reports of retinal thrombosis associated with the use of oral contraceptives that may lead to partial or complete loss of vision. Oral contraceptives should be discontinued if there is unexplained partial or complete loss of vision; onset of proptosis or diplopia; papilledema; or retinal vascular lesions. Appropriate diagnostic and therapeutic measures should be undertaken immediately.

6. Oral-Contraceptive Use Before or During Early Pregnancy

Extensive epidemiological studies have revealed no increased risk of birth defects in infants born to women who have used oral contraceptives prior to pregnancy. Studies also do not suggest a teratogenic effect, particularly insofar as cardiac anomalies and limb-reduction defects are concerned, when taken inadvertently during early pregnancy (see CONTRAINDICATIONS).

It is recommended that for any patient who has missed two consecutive periods, pregnancy should be ruled out. If the patient has not adhered to the prescribed schedule, the possibility of pregnancy should be considered at the time of the first missed period. Oral-contraceptive use should be discontinued if pregnancy is confirmed.

7. Gallbladder Disease

Combination oral contraceptives may worsen existing gallbladder disease and may accelerate the development of this disease in previously asymptomatic women. Earlier studies have reported an increased lifetime relative risk of gallbladder surgery in users of oral contraceptives and estrogens. More recent studies, however, have shown that the relative risk of developing gallbladder disease among oral-contraceptive users may be minimal. The recent findings of minimal risk may be related to the use of oral-contraceptive formulations containing lower hormonal doses of estrogens and progestogens. A past history of COC-related cholestasis predicts an increased risk with subsequent COC use. Women with a history of pregnancy-related cholestasis may be at an increased risk for COC related cholestasis.

8. Carbohydrate and Lipid Metabolic Effects

Oral contraceptives have been shown to cause glucose intolerance in a significant percentage of users. Carefully monitor females with prediabetes and diabetes who are using Lutera. Lutera may decrease glucose tolerance.

A small proportion of women will have persistent hypertriglyceridemia while on the COCs. As discussed earlier (see WARNINGS and PRECAUTIONS), changes in serum triglycerides and lipoprotein levels have been reported in oral-contraceptive users.

9. Elevated Blood Pressure

Lutera is contraindicated in women with uncontrolled hypertension or hypertension with vascular disease (see CONTRAINDICATIONS). For all females, including those with well-controlled hypertension, monitor blood pressure at routine visits and stop Lutera if blood pressure rises significantly.
An increase in blood pressure has been reported in females using CHCs, and this increase is more likely in older women with extended duration of use. The effect of CHCs on blood pressure may vary according to the progestin in the CHC.

10. Headache

Lutera is contraindicated in females who have headaches with focal neurological symptoms or have migraine headaches with aura, and in women over age 35 years who have migraine head aches with or without aura.

The onset or exacerbation of migraine or development of headache with a new pattern that is recurrent, persistent, or severe requires discontinuation of oral contraceptives and evaluation of the cause. Consider discontinuation of Lutera if there is an increased frequency or severity of migraines during CHC use (which may be prodromal of a cerebrovascular event; see WARNINGS and CONTRAINDICATIONS.)

11. Bleeding Irregularities

Unscheduled bleeding and spotting are sometimes encountered in patients on oral contraceptives, especially during the first three months of use. The type and dose of progestogen may be important. If bleeding persists or recurs, nonhormonal causes should be considered and adequate diagnostic measures taken to rule out malignancy or pregnancy in the event of unscheduled bleeding, as in the case of any abnormal vaginal bleeding. If pathology has been excluded, time or a change to another formulation may solve the problem. In the event of amenorrhea, pregnancy should be ruled out.

Some women may encounter post-pill amenorrhea or oligomenorrhea (possibly with anovulation), especially when such a condition was preexistent.

In the clinical trial with levonorgestrel 0.1 mg and ethinyl estradiol 0.02 mg tablets, unscheduled bleeding was defined as bleeding or spotting that occurred:
• During cycle 1 on pill-pack Days 4 to 21, inclusive of a 28-day cycle.
• In subsequent cycles, on Days 5 to 21 inclusive or on pill-pack Days 1 to 4 inclusive if preceded by 2 consecutive days without bleeding or spotting.
Based on subject diaries, the proportion of subjects reporting unscheduled bleeding or spotting per 28-day cycle decreased over time: 30.5% at Cycle 1 versus 18.2% at Cycle 12.

12. Hereditary Angioedema

In women with hereditary angioedema, exogenous estrogens may induce or exacerbate symptoms of angioedema.

13. Chloasma

Chloasma may occur, especially in women with a history of chloasma gravidarum. Advise women with a history of chloasma to avoid exposure to the sun or ultraviolet radiation while taking Lutera.

14. Effect on Binding Globulins

The estrogen component of COCs may raise the serum concentrations of thyroxine-binding globulin, sex hormone-binding globulin, and cortisol-binding globulin. Monitor thyroid-stimulating hormone (TSH) levels for females receiving Lutera and thyroid hormone replacement therapy concomitantly. Follow the recommendation for the thyroid hormone in accordance with its Prescribing Information.

PRECAUTIONS

1. General

Patients should be counseled that oral contraceptives do not protect against transmission of HIV (AIDS) and other sexually transmitted diseases (STDs) such as chlamydia, genital herpes, genital warts, gonorrhea, hepatitis B, and syphilis.

This product contains FD&C Yellow No. 5 (tartrazine) which may cause allergic-type reactions (including bronchial asthma) in certain susceptible persons. Although the overall incidence of FD&C Yellow No. 5 (tartrazine) sensitivity in the general population is low, it is frequently seen in patients who also have aspirin hypersensitivity.

2. Physical Examination and Follow-Up

A periodic personal and family medical history and complete physical examination are appropriate for all women, including women using oral contraceptives. The physical examination, however, may be deferred until after initiation of oral contraceptives if requested by the woman and judged appropriate by the clinician. The physical examination should include special reference to blood pressure, breasts, abdomen, pelvic organs, and relevant laboratory tests. In case of undiagnosed, persistent, or recurrent abnormal vaginal bleeding, appropriate diagnostic measures should be conducted to rule out malignancy. Women with a strong family history of breast cancer or who have breast nodules should be monitored with particular care.

3. Lipid Disorders

Women who are being treated for hyperlipidemias should be followed closely if they elect to use oral contraceptives. Some progestogens may elevate LDL levels and may render the control of hyperlipidemias more difficult. (See WARNINGS)

A small proportion of women will have adverse lipid changes while taking oral contraceptives. Nonhormonal contraception should be considered in women with uncontrolled dyslipidemias. Persistent hypertriglyceridemia may occur in a small population of combination oral contraceptive users. Elevations of plasma triglycerides may lead to pancreatitis and other complications.

4. Liver Function

If jaundice develops in any woman receiving such drugs, the medication should be discontinued. Steroid hormones may be poorly metabolized in patients with impaired liver function.

5. Fluid Retention

Oral contraceptives may cause some degree of fluid retention. They should be prescribed with caution, and only with careful monitoring, in patients with conditions which might be aggravated by fluid retention.

6. Depression

Monitor females with a history of depression and discontinue Lutera if depression recurs to a serious degree. Data on the association of CHCs with onset of depression or exacerbation of existing depression are limited.

7. Contact Lenses

Contact-lens wearers who develop visual changes or changes in lens tolerance should be assessed by an ophthalmologist.

8. Gastrointestinal

Diarrhea and/or vomiting may reduce hormone absorption resulting in decreased serum concentrations. If a patient vomits or has diarrhea after taking an active tablet, instruct the patient to not take an additional active tablet on that day and to continue the regimen the next day as prescribed. In case of vomiting or diarrhea that continues for 48 hours or greater, instruct the patient to contact the health care provider and use back-up or alternative contraception until active tablets have been taken for 7 consecutive days after vomiting and diarrhea have resolved.

9. Drug Interactions

Concomitant Use with HCV Combination Therapy-Liver Enzyme Elevation

Do not co-administer Lutera with HCV drug combinations containing ombitasvir/paritaprevir/ritonavir, with or without dasabuvir, due to potential for ALT elevations (see WARINGS, RISK OF LIVER ENZYME ELEVATIONS WITH CONCOMITANT HEPATITIS C TREATMENT).

Changes in Contraceptive Effectiveness Associated with Coadministration of Other Products:

Contraceptive effectiveness may be reduced when hormonal contraceptives are coadministered with antibiotics, anticonvulsants, and other drugs that increase the metabolism of contraceptive steroids. This could result in unintended pregnancy or breakthrough bleeding. Examples include rifampin, rifabutin, barbiturates, primidone, phenylbutazone, phenytoin, dexamethasone, carbamazepine, felbamate, oxcarbazepine, topiramate, griseofulvin, and modafinil. In such cases a back-up nonhormonal method of birth control should be considered.

Several of the anti-HIV protease inhibitors have been studied with co-administration of oral combination hormonal contraceptives; significant changes (increase and decrease) in the plasma levels of the estrogen and progestin have been noted in some cases. The safety and efficacy of oral contraceptive products may be affected with coadministration of anti-HIV protease inhibitors. Healthcare providers should refer to the label of the individual anti-HIV protease inhibitors for further drug-drug interaction information.

Herbal products containing St. John's Wort (Hypericum perforatum) may induce hepatic enzymes (cytochrome P 450) and p-glycoprotein transporter and may reduce the effectiveness of contraceptive steroids. This may also result in breakthrough bleeding.

Increase in Plasma Levels Associated with Co-Administered Drugs:

Co-administration of atorvastatin and certain oral contraceptives containing ethinyl estradiol increases AUC values for ethinyl estradiol by approximately 20%. Ascorbic acid and acetaminophen increase the bioavailability of ethinyl estradiol since these drugs act as competitive inhibitors for sulfation of ethinyl estradiol in the gastrointestinal wall, a known pathway of elimination for ethinyl estradiol. CYP 3A4 inhibitors such as indinavir, itraconazole, ketoconazole, fluconazole, and troleandomycin may increase plasma hormone levels. Troleandomycin may also increase the risk of intrahepatic cholestasis during coadministration with combination oral contraceptives.

Changes in Plasma Levels of Co-Administered Drugs:

Combination hormonal contraceptives containing some synthetic estrogens (eg, ethinyl estradiol) may inhibit the metabolism of other compounds. Increased plasma concentrations of cyclosporin, prednisolone and other corticosteroids, and theophylline have been reported with concomitant administration of oral contraceptives. Decreased plasma concentrations of acetaminophen and increased clearance of temazepam, salicylic acid, morphine, and clofibric acid, due to induction of conjugation (particularly glucuronidation), have been noted when these drugs were administered with oral contraceptives. Concomitant use of Lutera may decrease lamotrigine exposure, which may reduce efficacy of lamotrigine. Adjust lamotrigine dosage as recommended in its Prescribing Information based on Lutera initiation or discontinuation.
Concomitant use of Lutera may increase thyroid-binding globulin concentration. Monitor thyroid-stimulating hormone (TSH) level and follow the recommendation for the thyroid hormone in accordance with its Prescribing Information.

The prescribing information of concomitant medications should be consulted to identify potential interactions.

10. Interactions with Laboratory Tests

Certain endocrine- and liver-function tests and blood components may be affected by oral contraceptives:

a. Increased prothrombin and factors VII, VIII, IX, and X; decreased antithrombin 3; increased norepinephrine-induced platelet aggregability.

b. Increased thyroid-binding globulin (TBG) leading to increased circulating total thyroid hormone, as measured by protein-bound iodine (PBI), T4 by column or by radioimmunoassay.

c. Other binding proteins may be elevated in serum i.e., corticosteroid binding globulin (CBG), sex hormone-binding globulins (SHBG) leading to increased levels of total circulating corticosteroids and sex steroids respectively.

d. Triglycerides may be increased and levels of various other lipids and lipoproteins may be affected.

e. Glucose tolerance may be decreased.

f. Serum folate levels may be depressed by oral-contraceptive therapy. This may be of clinical significance if a woman becomes pregnant shortly after discontinuing oral contraceptives.

11. Carcinogenesis

See WARNINGS section.

12. Pregnancy

Risk Summary

There is no use for contraception in pregnancy; therefore, Lutera should be discontinued during pregnancy. Epidemiologic studies and meta-analyses have not found an increased risk of genital or nongenital birth defects (including cardiac anomalies and limb-reduction defects) following exposure to COCs before conception or during early pregnancy.
In the U.S. general population, the estimated background risk of major birth defects and miscarriage in clinically recognized pregnancies is 2 to 4 percent and 15 to 20 percent, respectively.

Data
Human Data
Epidemiologic studies and meta-analyses have not found an increased risk of genital or nongenital birth defects (including cardiac anomalies and limb-reduction defects) following exposure to COCs before conception or during early pregnancy.

13. Lactation

Contraceptive hormones and metabolites are present in human milk. CHCs can reduce milk production in breast-feeding females. This reduction can occur at any time but is less likely to occur once breast-feeding is well-established. The developmental and health benefits of breast-feeding should be considered along with the mother’s clinical need for Lutera and any potential adverse effects on the breast-fed child from Lutera or from the underlying maternal condition.

14. Pediatric Use

Safety and efficacy of levonorgestrel and ethinyl estradiol tablets have been established in women of reproductive age. Safety and efficacy are expected to be the same for postpubertal adolescents under the age of 16 and for users 16 years and older. Use of levonorgestrel and ethinyl estradiol tablets before menarche is not indicated.

15. Geriatric Use

Levonorgestrel and ethinyl estradiol tablets have not been studied in women over 65 years of age and is not indicated in this population.

16. Body Mass Index

The safety and effectiveness of Lutera in females with a BMI > 35 kg/m^2 have not been adequately evaluated.

17. Information for the Patient

See Patient Labeling Printed Below.

ADVERSE REACTIONS

To report SUSPECTED ADVERSE REACTIONS, contact Dr. Reddy’s Laboratories Inc, at 1-888-375-3784 or FDA at 1-800-FDA-1088 or www.fda.gov/medwatch.

An increased risk of the following serious adverse reactions (see WARNINGS section for additional information) has been associated with the use of oral contraceptives:

Thromboembolic and thrombotic disorders and other vascular problems (including thrombophlebitis and venous thrombosis with or without pulmonary embolism, mesenteric thrombosis, arterial thromboembolism, myocardial infarction, cerebral hemorrhage, cerebral thrombosis), carcinoma of the reproductive organs and breasts, hepatic neoplasia (including hepatic adenomas or benign liver tumors), ocular lesions (including retinal vascular thrombosis), gallbladder disease, carbohydrate and lipid effects, elevated blood pressure, and headache including migraine.

Five studies that compared breast cancer risk between ever-users (current or past use) of COCs and never-users of COCs reported no association between ever use of COCs and breast cancer risk, with effect estimates ranging from 0.90 - 1.12 (Figure 2).

Three studies compared breast cancer risk between current or recent COC users (<6 months since last use) and never users of COCs (Figure 2). One of these studies reported no association between breast cancer risk and COC use. The other two studies found an increased relative risk of 1.19 - 1.33 with current or recent use. Both of these studies found an increased risk of breast cancer with current use of longer duration, with relative risks ranging from 1.03 with less than one year of COC use to approximately 1.4 with more than 8-10 years of COC use.

FIGURE 2: Relevant Studies of Risk of Breast Cancer with Combined Oral Contraceptives

RR = relative risk; OR = odds ratio; HR = hazard ratio. “ever COC” are females with current or past COC use; “never COC use” are females that never used COCs.

The following adverse reactions associated with the use of oral CHCs were identified in clinical studies or postmarketing reports. Because some of these reactions were reported voluntarily from a population of uncertain size, it is not always possible to reliably estimate their frequency or establish a causal relationship to drug exposure. Common adverse reactions associated with oral CHCs are headache, abdominal pain, nausea, metrorrhagia, vaginal moniliasis and pain, acne, and vaginitis.

Additional adverse reactions that have been reported include the following:

Eye disorder: intolerance to contact lenses, steepening of corneal curvature

Gastrointestinal disorders: Abdominal bloating, vomiting

General disorders and administration site conditions: Edema, fluid retention

Hepatobiliary disorders: Cholestatic jaundice

Pyschiatric disorders: Change in libido, mood changes

Reproductive system and breast disorders: Amenorrhea, breast tenderness, breast pain, breast enlargement, increased cervical mucous, change in menstrual flow, unscheduled bleeding

Skin and subcutaneous tissue disorders: Acne, melasma

Vascular disorders: Budd-Chiari syndrome, aggravation of varicose veins

OVERDOSAGE

Symptoms of oral contraceptive overdosage in adults and children may include nausea, vomiting, and drowsiness/fatigue; withdrawal bleeding may occur in females. There is no specific antidote and further treatment of overdose, if necessary, is directed to the symptoms.

DOSAGE AND ADMINISTRATION

To achieve maximum contraceptive effectiveness, Lutera® (levonorgestrel and ethinyl estradiol tablets USP) must be taken exactly as directed and at intervals not exceeding 24 hours. The dosage of Lutera is one orange tablet daily for 21 consecutive days, followed by one white inert tablet daily for 7 consecutive days, according to the prescribed schedule. It is recommended that Lutera tablets be taken at the same time each day.

During The First Cycle Of Use

The possibility of ovulation and conception prior to initiation of medication should be considered. The patient should be instructed to begin taking Lutera on either the first Sunday after the onset of menstruation (Sunday Start) or on Day 1 of menstruation (Day 1 Start).

Sunday start:

The patient is instructed to begin taking Lutera on the first Sunday after the onset of menstruation. If menstruation begins on a Sunday, the first tablet (orange) is taken that day. One orange tablet should be taken daily for 21 consecutive days, followed by one white inert tablet daily for 7 consecutive days. Withdrawal bleeding should usually occur within 3 days following discontinuation of orange tablets and may not have finished before the next pack is started. During the first cycle, contraceptive reliance should not be placed on Lutera until an orange tablet has been taken daily for 7 consecutive days, and a nonhormonal back-up method of birth control should be used during those 7 days.

Day 1 start:

During the first cycle of medication, the patient is instructed to begin taking Lutera during the first 24 hours of her period (day one of her menstrual cycle). One orange tablet should be taken daily for 21 consecutive days, followed by one white inert tablet daily for 7 consecutive days. Withdrawal bleeding should usually occur within 3 days following discontinuation of orange tablets and may not have finished before the next pack is started. If medication is begun on day one of the menstrual cycle, no back-up contraception is necessary. If Lutera tablets are started later than day one of the first menstrual cycle or postpartum, contraceptive reliance should not be placed on Lutera tablets until after the first 7 consecutive days of administration, and a nonhormonal back-up method of birth control should be used during those 7 days.

After the first cycle of use

The patient begins her next and all subsequent courses of tablets on the day after taking her last white tablet. She should follow the same dosing schedule: 21 days on orange tablets followed by 7 days on white tablets. If in any cycle the patient starts tablets later than the proper day, she should protect herself against pregnancy by using a nonhormonal back-up method of birth control until she has taken an orange tablet daily for 7 consecutive days.

Switching from another hormonal method of contraception

When the patient is switching from a 21-day regimen of tablets, she should wait 7 days after her last tablet before she starts Lutera. She will probably experience withdrawal bleeding during that week. She should be sure that no more than 7 days pass after her previous 21-day regimen. When the patient is switching from a 28-day regimen of tablets, she should start her first pack of Lutera on the day after her last tablet. She should not wait any days between packs. The patient may switch any day from a progestin-only pill and should begin Lutera the next day. If switching from an implant or injection, the patient should start Lutera on the day of implant removal or, if using an injection, the day the next injection would be due. In switching from a progestin-only pill, injection, implant, or intrauterine system (IUS), the patient should be advised to use additional nonhormonal contraception (such as condoms) until active tablets have been taken for 7 consecutive days of the first pack.

If spotting or breakthrough bleeding occurs

If spotting or breakthrough bleeding occur, the patient is instructed to continue on the same regimen. This type of bleeding is usually transient and without significance; however, if the bleeding is persistent or prolonged, the patient is advised to consult her physician.

Risk of pregnancy if tablets are missed

While there is little likelihood of ovulation occurring if only one or two orange tablets are missed, the possibility of ovulation increases with each successive day that scheduled orange tablets are missed. Although the occurrence of pregnancy is unlikely if Lutera is taken according to directions, if withdrawal bleeding does not occur, the possibility of pregnancy must be considered. If the patient has not adhered to the prescribed schedule (missed one or more tablets or started taking them on a day later than she should have), the probability of pregnancy should be considered at the time of the first missed period and appropriate diagnostic measures taken. If the patient has adhered to the prescribed regimen and misses two consecutive periods, pregnancy should be ruled out.

The risk of pregnancy increases with each active (orange) tablet missed. For additional patient instructions regarding missed tablets, see the WHAT TO DO IF YOU MISS PILLS section in the DETAILED PATIENT LABELING below.

Use after pregnancy, abortion or miscarriage

Lutera may be initiated no earlier than day 28 postpartum in the nonlactating mother or after a second trimester abortion due to the increased risk for thromboembolism (see CONTRAINDICATIONS, WARNINGS, and PRECAUTIONS concerning thromboembolic disease). The patient should be advised to use aadditional nonhormonal contraception (such as condoms) until active tablets have been taken for 7 consecutive days.

Lutera may be initiated immediately after a first trimester abortion or miscarriage. Instruct the patient to use additional nonhormonal contraception (such as condoms) until active tablets have been taken for 7 consecutive days, unless starting Lutera on the day of surgical abortion.

HOW SUPPLIED

Lutera® (Levonorgestrel and Ethinyl Estradiol Tablets, USP, 0.1 mg/0.02 mg) is available in a compact blister card (NDC 55741-005-28), containing 28 tablets arranged in 3 rows of 7 active tablets and 1 row of inert tablets, as follows:

21 active tablets: orange, round tablet debossed with "A3" on one side.

7 inert tablets: white, round tablet debossed with "P" on one side and "N" on the other side.

Lutera® Tablets are available in the following configuations

Carton of 6 NDC 55741-005-06

Store at 20° to 25°C (68° to 77°F), excursions permitted to 15ºC to 30ºC (59ºF to 86ºF). [See USP controlled room temperature].

Distributed by: Dr. Reddy’s Laboratories Inc.
Princeton, NJ 08540
Product of China

I 0221

Rev. A

Rev. 11/2025

Brief Summary Patient Package Insert

This product (like all oral contraceptives) is intended to prevent pregnancy. Oral contraceptives do not protect against transmission of HIV (AIDS) and other sexually transmitted diseases (STDs) such as chlamydia, genital herpes, genital warts, gonorrhea, hepatitis B, and syphilis.

Oral contraceptives, also known as "birth-control pills" or "the pill", are taken to prevent pregnancy, and when taken correctly, have a failure rate of approximately 1.0% per year (1 pregnancy per 100 women per year of use) when used without missing any pills. The average failure rate of large numbers of pill users is approximately 5% per year (5 pregnancies per 100 women per year of use) when women who miss pills are included. For most women oral contraceptives are also free of serious or unpleasant side effects. However, forgetting to take pills considerably increases the chances of pregnancy.

For the majority of women, oral contraceptives can be taken safely. But there are some women who are at high risk of developing certain serious diseases that can be life-threatening or may cause temporary or permanent disability or death. The risks associated with taking oral contraceptives increase significantly if you:

- smoke.
- have high blood pressure, diabetes, high cholesterol, or a tendency to form blood clots.
- have or have had clotting disorders, heart attack, stroke, angina pectoris, cancer of the breast or sex organs, jaundice, malignant or benign liver tumors, or major surgery with prolonged immobilization.
- have headaches with neurological symptoms.

You should not take the pill if you take any Hepatitis C drug combination containing ombitasvir/paritaprevir/ ritonavir, with or without dasabuvir. This may increase levels of the liver enzyme "alanine aminotransferase" (ALT) in the blood.

You should not take the pill if you suspect you are pregnant or have unexplained vaginal bleeding.

Although cardiovascular disease risks may be increased with oral-contraceptive use after age 40 in healthy, nonsmoking women, there are also greater potential health risks associated with pregnancy in older women.

WARNING: CIGARETTE SMOKING AND SERIOUS CARDIOVASCULAR EVENTS
Cigarette smoking increases the risk of serious cardiovascular events from combined oral contraceptives (COC) use. This risk increases with age, particularly in women over 35 years of age, and with the number of cigarettes smoked. For this reason, COCs, including Lutera, are contraindicated in women who are over 35 years of age and smoke (see CONTRAINDICATIONS and WARNINGS).

Most side effects of the pill are not serious. The most common such effects are nausea, vomiting, bleeding between menstrual periods, weight gain, breast tenderness, and difficulty wearing contact lenses. These side effects, especially nausea and vomiting, may subside within the first three months of use.

The serious side effects of the pill occur very infrequently, especially if you are in good health and do not smoke. However, you should know that the following medical conditions have been associated with or made worse by the pill:

1. Blood clots in the legs (thrombophlebitis) and lungs (pulmonary embolism), blockage or rupture of a blood vessel in the brain (stroke), blockage of blood vessels in the heart (heart attack and angina pectoris) or other organs of the body. As mentioned above, smoking increases the risk of heart attacks and strokes and subsequent serious medical consequences. Women with migraine also may be at increased risk of stroke with pill use.

2. Liver tumors, which may rupture and cause severe bleeding. A possible but not definite association has been found with the pill and liver cancer. However, liver cancers are extremely rare. The chance of developing liver cancer from using the pill is thus even rarer.

3. High blood pressure, although blood pressure usually returns to normal when the pill is stopped.

The symptoms associated with these serious side effects are discussed in the detailed leaflet given to you with your supply of pills. Notify your health-care provider if you notice any unusual physical disturbances while taking the pill. In addition, drugs such as rifampin, as well as some anticonvulsants and some antibiotics, herbal preparations containing St. John's Wort (Hypericum perforatum), and HIV/AIDS drugs may decrease oral-contraceptive effectiveness.

There may be slight increases in the risk of breast cancer among current users of hormonal birth control pills with longer duration of use of 8 years or more.

Some studies have found an increase in the incidence of cancer of the cervix in women who use oral contraceptives. However, this finding may be related to factors other than the use of oral contraceptives.

Be sure to discuss any medical condition you may have with your health-care provider. Your health-care provider will take a medical and family history before prescribing oral contraceptives and will examine you. The physical examination may be delayed to another time if you request it and the health-care provider believes that it is appropriate to postpone it. You should be reexamined at least once a year while taking oral contraceptives. The detailed patient information leaflet gives you further information which you should read and discuss with your health-care provider.

HOW TO TAKE LUTERA

IMPORTANT POINTS TO REMEMBER

BEFORE YOU START TAKING LUTERA:

1. BE SURE TO READ THESE DIRECTIONS:

Before you start taking Lutera.

And

Anytime you are not sure what to do.

2. THE RIGHT WAY TO TAKE THE PILL IS TO TAKE ONE PILL EVERY DAY AT THE SAME TIME.

If you miss pills you could get pregnant. This includes starting the pack late. The more pills you miss, the more likely you are to get pregnant. See "WHAT TO DO IF YOU MISS PILLS" below.

3. MANY WOMEN HAVE SPOTTING OR LIGHT BLEEDING, OR MAY FEEL SICK TO THEIR STOMACH DURING THE FIRST 1-3 PACKS OF PILLS.

If you feel sick to your stomach, do not stop taking Lutera. The problem will usually go away. If it doesn't go away, check with your health-care provider.

4. MISSING PILLS CAN ALSO CAUSE SPOTTING OR LIGHT BLEEDING, even when you make up these missed pills.

On the days you take 2 pills to make up for missed pills, you could also feel a little sick to your stomach.

5. IF YOU HAVE VOMITING (within 4 hours after you take your pill), you should follow the instructions for WHAT TO DO IF YOU MISS PILLS. IF YOU HAVE DIARRHEA or IF YOU TAKE SOME MEDICINES, including some antibiotics, your pills may not work as well.

Use a back-up nonhormonal method (such as condoms or spermicide) until you check with your health-care provider.

6. IF YOU HAVE TROUBLE REMEMBERING TO TAKE THE PILL, talk to your health-care provider about how to make pill-taking easier or about using another method of birth control.

7. IF YOU HAVE ANY QUESTIONS OR ARE UNSURE ABOUT THE INFORMATION IN THIS LEAFLET, call your health-care provider.

BEFORE YOU START TAKING LUTERA

1. DECIDE WHAT TIME OF DAY YOU WANT TO TAKE YOUR PILL. It is important to take it at about the same time every day.

2. LOOK AT YOUR PILL PACK.

The 28-pill pack has 21 "active" orange pills (with hormones) to take for 3 weeks, followed by 1 week of reminder white pills (without hormones).

3. FIND:

1) where on the pack to start taking pills,

2) in what order to take the pills (follow the arrows), and

3) the week numbers as shown in the picture below.

4. BE SURE YOU HAVE READY AT ALL TIMES:

ANOTHER KIND OF BIRTH CONTROL (such as condoms or spermicide) to use as a back-up in case you miss pills.

AN EXTRA, FULL PILL PACK.

For use of day labels, see WHEN TO START THE FIRST PACK OF PILLS below.

WHEN TO START THE FIRST PACK OF PILLS

You have a choice of which day to start taking your first pack of pills.

Decide with your health-care provider which is the best day for you. Pick a time of day which will be easy to remember.

DAY 1 START

1. Pick the day label sticker that starts with the first day of your period. Place this day label sticker over the area that has the days of the week (starting with Sunday) pre-printed on the tablet dispenser.

Note: if the first day of your period is a Sunday, you can skip step #1.

2. Take the first "active" orange pill of the first pack during the first 24 hours of your period.

3. You will not need to use a back-up nonhormonal method of birth control, since you are starting the pill at the beginning of your period.

SUNDAY START

1. Take the first "active" orange pill of the first pack on the Sunday after your period starts, even if you are still bleeding. If your period begins on Sunday, start the pack that same day.

2. Use a nonhormonal method of birth control (such as condoms or spermicide) as a back-up method if you have sex anytime from the Sunday you start your first pack until the next Sunday (7 days).

WHAT TO DO DURING THE MONTH

1. Take one pill at the same time every day until the pack is empty.

Do not skip pills even if you are spotting or bleeding between monthly periods or feel sick to your stomach (nausea).

Do not skip pills even if you do not have sex very often.

2. When you finish a pack:

Start the next pack on the day after your last "reminder" pill. Do not wait any days between packs.

IF YOU SWITCH FROM ANOTHER BRAND OR COMBINATION PILLS

If your previous brand had 21 pills: Wait 7 days to start taking Lutera. You will probably have your period during that week. Be sure that no more than 7 days pass between the 21-day pack and taking the first orange Lutera pill ("active" with hormone).

If your previous brand had 28 pills: Start taking the first orange Lutera pill ("active" with hormone) on the day after your last reminder pill. Do not wait any days between packs.

WHAT TO DO IF YOU MISS PILLS

Lutera may not be as effective if you miss orange "active" pills, and particularly if you miss the first few or the last few orange "active" pills in a pack.

If you MISS 1 orange "active" pill:

1. Take it as soon as you remember. Take the next pill at your regular time. This means you may take 2 pills in 1 day.

2. You COULD BECOME PREGNANT if you have sex in the 7 days after you restart your pills. You MUST use a nonhormonal birth-control method (such as condoms or spermicide) as a back-up for those 7 days.

If you MISS 2 orange "active" pills in a row in WEEK 1 OR WEEK 2 of your pack:

1. Take 2 pills on the day you remember and 2 pills the next day.

2. Then take 1 pill a day until you finish the pack.

3. You COULD BECOME PREGNANT if you have sex in the 7 days after you restart your pills. You MUST use a nonhormonal birth-control method (such as condoms or spermicide) as a back-up for those 7 days.

If you MISS 2 orange "active" pills in a row in THE 3rd WEEK:

1. If you are a Day 1 Starter:

THROW OUT the rest of the pill pack and start a new pack that same day.

If you are a Sunday Starter:

Keep taking 1 pill every day until Sunday.

On Sunday, THROW OUT the rest of the pack and start a new pack of pills that same day.

2. You may not have your period this month but this is expected

However, if you miss your period 2 months in a row, call your health-care provider because you might be pregnant.

3. You COULD BECOME PREGNANT if you have sex in the 7 days after you restart your pills. You MUST use a nonhormonal birth-control method (such as condoms or spermicide) as a back-up for those 7 days.

If you MISS 3 OR MORE orange "active" pills in a row (during the first 3 weeks):

1. If you are a Day 1 Starter:

THROW OUT the rest of the pill pack and start a new pack that same day.

If you are a Sunday Starter:

Keep taking 1 pill every day until Sunday.

On Sunday, THROW OUT the rest of the pack and start a new pack of pills that same day.

2. You may not have your period this month but this is expected.

However, if you miss your period 2 months in a row, call your health-care provider because you might be pregnant.

3. You COULD BECOME PREGNANT if you have sex in the 7 days after you restart your pills. You MUST use a nonhormonal birth-control method (such as condoms or spermicide) as a back-up for those 7 days.

If you forget any of the 7 white "reminder" pills in Week 4:

THROW AWAY the pills you missed.

Keep taking 1 pill each day until the pack is empty.

You do not need a back-up nonhormonal birth-control method if you start your next pack on time.

FINALLY, IF YOU ARE STILL NOT SURE WHAT TO DO ABOUT THE PILLS YOU HAVE MISSED

Use a BACK-UP NONHORMONAL BIRTH-CONTROL METHOD anytime you have sex.

KEEP TAKING ONE PILL EACH DAY until you can reach your health-care provider.

BIRTH CONTROL AFTER STOPPING THE PILL

If you do not wish to become pregnant after stopping the pill, speak to your health-care provider about another method of birth control.

DETAILED PATIENT LABELING

This product (like all oral contraceptives) is intended to prevent pregnancy. Oral contraceptives do not protect against transmission of HIV (AIDS) and other sexually transmitted diseases (STDs) such as chlamydia, genital herpes, genital warts, gonorrhea, hepatitis B, and syphilis.

INTRODUCTION

Any woman who considers using oral contraceptives (the "birth-control pill" or "the pill") should understand the benefits and risks of using this form of birth control. This leaflet will give you much of the information you will need to make this decision and will also help you determine if you are at risk of developing any of the serious side effects of the pill. It will tell you how to use the pill properly so that it will be as effective as possible. However, this leaflet is not a replacement for a careful discussion between you and your health-care provider. You should discuss the information provided in this leaflet with him or her, both when you first start taking the pill and during your revisits. You should also follow your health-care provider's advice with regard to regular check-ups while you are on the pill.

EFFECTIVENESS OF ORAL CONTRACEPTIVES

Oral contraceptives or "birth-control pills" or "the pill" are used to prevent pregnancy and are more effective than most other nonsurgical methods of birth control. When they are taken correctly, without missing any pills, the chance of becoming pregnant is approximately 1% per year (1 pregnancy per 100 women per year of use). Typical failure rates are approximately 5% per year (5 pregnancies per 100 women per year of use) when women who miss pills are included. The chance of becoming pregnant increases with each missed pill during each 28-day cycle of use.

In comparison, average failure rates for other methods of birth control during the first year of use are as follows:

IUD:0.1-2%

Depo-Provera® (injectable progestogen): 0.3%

Norplant® System (levonorgestrel implants): 0.05%

Diaphragm with spermicides: 20%

Spermicides alone: 26%

Male condom alone: 14%

Female condom alone: 21%

Cervical cap

Never given birth: 20%

Given birth: 40%

Periodic abstinence: 25%

No methods: 85%

WHO SHOULD NOT TAKE ORAL CONTRACEPTIVES

WARNING: CIGARETTE SMOKING AND SERIOUS CARDIOVASCULAR EVENTS
Cigarette smoking increases the risk of serious cardiovascular events from combined oral contraceptives (COC) use. This risk increases with age, particularly in women over 35 years of age, and with the number of cigarettes smoked. For this reason, COCs, including Lutera, are contraindicated in women who are over 35 years of age and smoke.

Some women should not use the pill. For example, you should not take the pill if you have any of the following conditions:

- History of heart attack or stroke.
- Blood clots in the legs (thrombophlebitis), lungs (pulmonary embolism), or eyes.
- A history of blood clots in the deep veins of your legs.
- A problem with your blood that makes it clot more than normal.
- Chest pain (angina pectoris).
- Known or suspected breast cancer or cancer sensitive to female hormones
- Unexplained vaginal bleeding (until a diagnosis is reached by your health-care provider).
- Liver tumor (benign or cancerous) or active liver disease.
- Yellowing of the whites of the eyes or of the skin (jaundice) during pregnancy or during previous use of the pill.
- Known or suspected pregnancy.
- A need for surgery with prolonged bedrest.
- Heart valve or heart rhythm disorders that may be associated with formation of blood clots.
- Diabetes affecting your circulation.
- Certain kinds of severe migraine headaches with aura, numbness, weakness or changes in vision, or any migraine headaches if you are over 35 years of age.
- Uncontrolled high blood pressure.

Tell your health-care provider if you have had any of these conditions. Your health-care provider can recommend another method of birth control.

You should not take the pills if you take any Hepatitis C drug combination containing ombitasvir/paritaprevir/ritonavir, with or without dasabuvir. This may increase levels of the liver enzyme "alanine aminotransferase" (ALT) in the blood.

OTHER CONSIDERATIONS BEFORE TAKING ORAL CONTRACEPTIVES

Tell your health-care provider if you have ever had:

- An abnormal mammogram.
- Diabetes.
- Elevated cholesterol or triglycerides.
- High blood pressure.
- A tendency to form blood clots.
- Migraine or other headaches or epilepsy.
- Depression.
- Gallbladder, liver, heart, or kidney disease.
- History of scanty or irregular menstrual periods.

Women with any of these conditions should be checked often by their health-care provider if they choose to use oral contraceptives. Also, be sure to inform your health-care provider if you smoke or are on any medications.

Although cardiovascular disease risks may be increased with oral contraceptive use in healthy, non-smoking women over 40 (even with the newer low-dose formulations), there are also greater potential health risks associated with pregnancy in older women.

RISKS OF TAKING ORAL CONTRACEPTIVES

1. Risks of developing blood clots

Blood clots and blockage of blood vessels are the most serious side effects of taking oral contraceptives and can cause death or serious disability. In particular, a clot in the legs can cause thrombophlebitis and a clot that travels to the lungs can cause a sudden blocking of the vessel carrying blood to the lungs. Rarely, clots occur in the blood vessels of the eye and may cause blindness, double vision, or impaired vision.

Users of combination oral contraceptives have a higher risk of developing blood clots compared to non-users. This risk is highest during the first year of combination oral-contraceptive use.

If you take oral contraceptives and need elective surgery, need to stay in bed for a prolonged illness or injury, or have recently delivered a baby, you may be at risk of developing blood clots. You should consult your health-care provider about stopping oral contraceptives three to four weeks before surgery and not taking oral contraceptives for two weeks after surgery or during bed rest. You should also not take oral contraceptives soon after delivery of a baby or after a mid-trimester pregnancy termination. It is advisable to wait for at least four weeks after delivery if you are not breast-feeding. If you are breast-feeding, you should wait until you have weaned your child before using the pill. (See also the section While breast-feeding in GENERAL PRECAUTIONS.)

The risk of blood clots is greater in users of combination oral contraceptives compared to nonusers. The risk of abnormal blood clotting increases with age in both users and nonusers of combination oral contraceptives, but the increased risk from the oral contraceptive appears to be present at all ages.

The excess risk of blood clots is highest during the first year a woman ever uses a combined oral contraceptive. This increased risk is lower than blood clots associated with pregnancy. The use of combination oral contraceptives also increases the risk of other clotting disorders, including heart attack and stroke. Blood clots in veins cause death in 1% to 2% of cases. The risk of clotting is further increased in women with other conditions. Examples include: smoking, high blood pressure, abnormal lipid levels, certain inherited or acquired clotting disorders, obesity, surgery or injury with prolonged inactivity or bedrest, recent delivery or second trimester abortion. Discuss with your healthcare provider whether combination oral contraceptives should be stopped before surgery with prolonged inactivity or bedrest.

Cigarette smoking increases the risk of serious cardiovascular events from COC use. This risk increases with age and amount of smoking and is quite pronounced in women over 35. Women who use combination oral contraceptives should be strongly advised not to smoke. If you smoke you should not use combination oral contraceptives.

2. Heart attacks and strokes

Oral contraceptives may increase the tendency to develop strokes or transient ischemic attacks (blockage or rupture of blood vessels in the brain) and angina pectoris and heart attacks (blockage of blood vessels in the heart). Any of these conditions can cause death or serious disability.

Smoking greatly increases the possibility of suffering heart attacks and strokes. Furthermore, smoking and the use of oral contraceptives greatly increase the chances of developing and dying of heart disease.

Women with migraine (especially migraine/headache with neurological symptoms) who take oral contraceptives also may be at higher risk of stroke and must not use combination oral contraceptives (see section WHO SHOULD NOT TAKE ORAL CONTRACEPTIVES).

3. Gallbladder disease

Oral-contraceptive users probably have a greater risk than nonusers of having gallbladder disease. Oral-contraceptives may worsen existing gallbladder disease or accelerate the development of gallbladder disease in women previously without symptoms.

4. Liver tumors

In rare cases, oral contraceptives can cause benign but dangerous liver tumors. These benign liver tumors can rupture and cause fatal internal bleeding. In addition, a possible but not definite association has been found with the pill and liver cancers in two studies in which a few women who developed these very rare cancers were found to have used oral contraceptives for long periods. However, liver cancers are extremely rare. The chance of developing liver cancer from using the pill is thus even rarer.

5. Risk of Cancer

It is not known if hormonal birth control pills causes breast cancer. Some studies, but not all, suggest that there could be a slight increase in the risk of breast cancer among current users with longer duration of use.

If you have breast cancer now, or have had it in the past, do not use hormonal birth control because some breast cancers are sensitive to hormones.

Some studies have found an increase in the incidence of cancer of the cervix in women who use oral contraceptives. However, this finding may be related to factors other than the use of oral contraceptives.

6. Lipid Metabolism and Pancreatitis

There have been reports of increases of blood cholesterol and triglycerides in users of combination oral contraceptives. Increases in triglycerides have led to inflammation of the pancreas (pancreatitis) in some cases.

WARNING SIGNALS

If any of these adverse effects occur while you are taking oral contraceptives, call your health-care provider immediately:

- Sharp chest pain, coughing of blood, or sudden shortness of breath (indicating a possible clot in the lung).
- Pain in the calf (indicating a possible clot in the leg).
- Crushing chest pain or heaviness in the chest (indicating a possible heart attack).
- Sudden severe headache or vomiting, dizziness or fainting, disturbances of vision or speech, weakness, or numbness in an arm or leg (indicating a possible stroke).
- Sudden partial or complete loss of vision (indicating a possible clot in the eye).
- Severe pain or tenderness in the stomach area (indicating a possibly ruptured liver tumor).
- Difficulty in sleeping, weakness, lack of energy, fatigue, or change in mood (possibly indicating severe depression).
- Jaundice or a yellowing of the skin or eyeballs, accompanied frequently by fever, fatigue, loss of appetite, dark-colored urine, or light-colored bowel movements (indicating possible liver problems).

SIDE EFFECTS OF ORAL CONTRACEPTIVES

1. Unscheduled or breakthrough vaginal bleeding or spotting

Unscheduled vaginal bleeding or spotting may occur while you are taking the pills. Unscheduled bleeding may vary from slight staining between menstrual periods to breakthrough bleeding which is a flow much like a regular period. Unscheduled bleeding occurs most often during the first few months of oral-contraceptive use, but may also occur after you have been taking the pill for some time. Such bleeding may be temporary and usually does not indicate any serious problems. It is important to continue taking your pills on schedule. If the bleeding occurs in more than one cycle or lasts for more than a few days, talk to your health-care provider.

2. Possible cancer that is sensitive to female hormones or possible cancer of the cervix

Women who have or have ever had breast cancer, or any cancer sensitive to female hormones – such as skin cancer (melanoma), lung cancer, and brain cancer, should not use Lutera. However, birth control pills do not seem to cause cancer.

Women who use birth control pills may have a slightly higher chance of getting cervical cancer. However, this may be due to other reasons, such as having more sexual partners.

3. Contact lenses

If you wear contact lenses and notice a change in vision or an inability to wear your lenses, contact your health-care provider.

4. Fluid retention

Oral contraceptives may cause edema (fluid retention) with swelling of the fingers or ankles and may raise your blood pressure. If you experience fluid retention, contact your health-care provider.

5. Melasma

A spotty darkening of the skin is possible, particularly of the face.

6. Other side effects

Other side effects may include nausea, breast tenderness, change in appetite, headache, nervousness, depression, dizziness, loss of scalp hair, rash, vaginal infections, inflammation of the pancreas, and allergic reactions.

If any of these side effects bother you, call your health-care provider.

GENERAL PRECAUTIONS

1. Missed periods and use of oral contraceptives before or during early pregnancy

There may be times when you may not menstruate regularly after you have completed taking a cycle of pills. If you have taken your pills regularly and miss one menstrual period, continue taking your pills for the next cycle but be sure to inform your health-care provider before doing so. If you have not taken the pills daily as instructed and missed a menstrual period, or if you missed two consecutive menstrual periods, you may be pregnant. Check with your health-care provider immediately to determine whether you are pregnant. Stop taking oral contraceptives if you are pregnant.

There is no conclusive evidence that oral-contraceptive use is associated with an increase in birth defects, when taken inadvertently during early pregnancy. Previously, a few studies had reported that oral contraceptives might be associated with birth defects, but these studies have not been confirmed. Nevertheless, oral contraceptives should not be used during pregnancy. You should check with your health-care provider about risks to your unborn child of any medication taken during pregnancy.

2. While breast-feeding

If you are breast-feeding, consult your health-care provider before starting oral contraceptives. Some of the drug will be passed on to the child in the milk. A few adverse effects on the child have been reported, including yellowing of the skin (jaundice) and breast enlargement. In addition, oral contraceptives may decrease the amount and quality of your milk. If possible, do not use oral contraceptives while breast-feeding. You should use another method of contraception since breast-feeding provides only partial protection from becoming pregnant and this partial protection decreases significantly as you breast-feed for longer periods of time. You should consider starting oral contraceptives only after you have weaned your child completely.

3. Laboratory tests

If you are scheduled for any laboratory tests, tell your doctor you are taking birth-control pills. Certain blood tests may be affected by birth-control pills.

4. Drug interactions

Certain drugs may interact with birth-control pills to make them less effective in preventing pregnancy or cause an increase in breakthrough bleeding. Such drugs include rifampin, drugs used for epilepsy such as barbiturates (for example, phenobarbital) and phenytoin (Dilantin® is one brand of this drug), primidone (Mysoline®), topiramate (Topamax®), carbamazepine (Tegretol® is one brand of this drug), phenylbutazone (Butazolidin® is one brand), some drugs used for HIV or AIDS such as ritonavir (Norvir®), modafinil (Provigil®) and possibly certain antibiotics (such as ampicillin and other penicillins, and tetracyclines), and herbal products containing St. John's Wort (Hypericum perforatum). You may also need to use a nonhormonal method of contraception during any cycle in which you take drugs that can make oral contraceptives less effective.

You may be at higher risk of a specific type of liver dysfunction if you take troleandomycin and oral contraceptives at the same time.

You should inform your health-care provider about all medicines you are taking, including nonprescription products.

5. Sexually transmitted diseases

This product (like all oral contraceptives) is intended to prevent pregnancy. It does not protect against transmission of HIV (AIDS) and other sexually transmitted diseases such as chlamydia, genital herpes, genital warts, gonorrhea, hepatitis B, and syphilis.

HOW TO TAKE LUTERA

IMPORTANT POINTS TO REMEMBER

BEFORE YOU START TAKING LUTERA:

1. BE SURE TO READ THESE DIRECTIONS:

Before you start taking Lutera.

And

Anytime you are not sure what to do.

2. THE RIGHT WAY TO TAKE THE PILL IS TO TAKE ONE PILL EVERY DAY AT THE SAME TIME.

If you miss pills you could get pregnant. This includes starting the pack late. The more pills you miss, the more likely you are to get pregnant. See "WHAT TO DO IF YOU MISS PILLS" below.

3. MANY WOMEN HAVE SPOTTING OR LIGHT BLEEDING, OR MAY FEEL SICK TO THEIR STOMACH DURING THE FIRST 1 TO 3 PACKS OF PILLS.

If you feel sick to your stomach, do not stop taking Lutera. The problem will usually go away. If it doesn't go away, check with your health-care provider.

4. MISSING PILLS CAN ALSO CAUSE SPOTTING OR LIGHT BLEEDING, even when you make up these missed pills.

On the days you take 2 pills to make up for missed pills, you could also feel a little sick to your stomach.

5. IF YOU HAVE VOMITING (within 4 hours after you take your pill), you should follow the instructions for WHAT TO IF YOU MISS PILLS. IF YOU HAVE DIARRHEA or IF YOU TAKE SOME MEDICINES, including some antibiotics, your pills may not work as well.

Use a back-up nonhormonal method (such as condoms or spermicide) until you check with your health-care provider.

6. IF YOU HAVE TROUBLE REMEMBERING TO TAKE THE PILL, talk to your health-care provider about how to make pill-taking easier or about using another method of birth control.

7. IF YOU HAVE ANY QUESTIONS OR ARE UNSURE ABOUT THE INFORMATION IN THIS LEAFLET, contact your health-care provider.

BEFORE YOU START TAKING LUTERA

1. DECIDE WHAT TIME OF DAY YOU WANT TO TAKE YOUR PILL. It is important to take it at about the same time every day.

2. LOOK AT YOUR PILL PACK.

The 28-pill pack has 21 "active" orange pills (with hormones) to take for 3 weeks, followed by 1 week of reminder white pills (without hormones).

3. FIND:

1) where on the pack to start taking pills,

2) in what order to take the pills (follow the arrows), and

3) the week numbers as shown in the picture below.

4. BE SURE YOU HAVE READY AT ALL TIMES:

ANOTHER KIND OF BIRTH CONTROL (such as condoms or spermicide) to use as a back-up in case you miss pills.

AN EXTRA, FULL PILL PACK.

For use of day labels, see WHEN TO START THE FIRST PACK OF PILLS below.

WHEN TO START THE FIRST PACK OF PILLS

You have a choice of which day to start taking your first pack of pills.

Decide with your health-care provider which is the best day for you. Pick a time of day which will be easy to remember.

DAY 1 START:

1. Pick the day label sticker that starts with the first day of your period. Place this day label sticker over the area that has the days of the week (starting with Sunday) pre-printed on the tablet dispenser.

Note: if the first day of your period is a Sunday, you can skip step #1.

2. Take the first "active" orange pill of the first pack during the first 24 hours of your period.

3. You will not need to use a back-up nonhormonal method of birth control, since you are starting the pill at the beginning of your period.

SUNDAY START:

1. Take the first "active" orange pill of the first pack on the Sunday after your period starts, even if you are still bleeding. If your period begins on Sunday, start the pack that same day.

2. Use a nonhormonal method of birth control (such as condoms or spermicide) as a back-up method if you have sex anytime from the Sunday you start your first pack until the next Sunday (7 days).

WHAT TO DO DURING THE MONTH

1. Take one pill at the same time every day until the pack is empty.

Do not skip pills even if you are spotting or bleeding between monthly periods or feel sick to your stomach (nausea).

Do not skip pills even if you do not have sex very often.

2. When you finish a pack:

Start the next pack on the day after your last "reminder" pill. Do not wait any days between packs.

IF YOU SWITCH FROM ANOTHER BRAND OR COMBINATION PILLS:

If your previous brand had 21 pills: Wait 7 days to start taking Lutera. You will probably have your period during that week. Be sure that no more than 7 days pass between the 21-day pack and taking the first orange Lutera pill ("active" with hormone).

If your previous brand had 28 pills: Start taking the first orange Lutera pill ("active" with hormone) on the day after your last reminder pill. Do not wait any days between packs.

WHAT TO DO IF YOU MISS PILLS

Lutera may not be as effective if you miss orange "active" pills, and particularly if you miss the first few or the last few orange "active" pills in a pack.

If you MISS 1 orange "active" pill:

1. Take it as soon as you remember. Take the next pill at your regular time. This means you may take 2 pills in 1 day.

If you MISS 2 orange "active" pills in a row in WEEK 1 OR WEEK 2 of your pack:

1. Take 2 pills on the day you remember and 2 pills the next day.

2. Then take 1 pill a day until you finish the pack.

3. You COULD BECOME PREGNANT if you have sex in the 7 days after you restart your pills. You MUST use a nonhormonal birth-control method (such as condoms or spermicide) as a back-up for those 7 days.

If you MISS 2 orange "active" pills in a row in THE 3rd WEEK:

1. If you are a Day 1 Starter:

THROW OUT the rest of the pill pack and start a new pack that same day.

If you are a Sunday Starter:

Keep taking 1 pill every day until Sunday.

On Sunday, THROW OUT the rest of the pack and start a new pack of pills that same day.

2. You may not have your period this month but this is expected

However, if you miss your period 2 months in a row, call your health-care provider because you might be pregnant.

3. You COULD BECOME PREGNANT if you have sex in the 7 days after you restart your pills. You MUST use a nonhormonal birth-control method (such as condoms or spermicide) as a back-up for those 7 days.

If you MISS 3 OR MORE orange "active" pills in a row (during the first 3 weeks):

1. If you are a Day 1 Starter:

THROW OUT the rest of the pill pack and start a new pack that same day.

If you are a Sunday Starter:

Keep taking 1 pill every day until Sunday.

On Sunday, THROW OUT the rest of the pack and start a new pack of pills that same day.

2. You may not have your period this month but this is expected.

However, if you miss your period 2 months in a row, call your health-care provider because you might be pregnant.

3. You COULD BECOME PREGNANT if you have sex in the 7 days after you restart your pills. You MUST use a nonhormonal birth-control method (such as condoms or spermicide) as a back-up for those 7 days.

If you forget any of the 7 white "reminder" pills in Week 4:

THROW AWAY the pills you missed.

Keep taking 1 pill each day until the pack is empty.

You do not need a back-up nonhormonal birth-control method if you start your next pack on time.

FINALLY, IF YOU ARE STILL NOT SURE WHAT TO DO ABOUT THE PILLS YOU HAVE MISSED

Use a BACK-UP NONHORMONAL BIRTH-CONTROL METHOD anytime you have sex.

KEEP TAKING ONE PILL EACH DAY until you can reach your health-care provider.

PREGANCY DUE TO PILL FAILURE

The incidence of pill failure resulting in pregnancy is approximately 1 per year (1 pregnancy per 100 women per year of use) if taken every day as directed, but the more typical failure rate is approximately 5% per year (5 pregnancies per 100 women per year of use) including women who do not always take the pill exactly as directed without missing any pills. If you do become pregnant, the risk to the fetus is minimal, but you should stop taking your pills and discuss the pregnancy with your health-care provider.

PREGNANCY AFTER STOPPING THE PILL

There may be some delay in becoming pregnant after you stop using oral contraceptives, especially if you had irregular menstrual cycles before you used oral contraceptives. It may be advisable to postpone conception until you begin menstruating regularly once you have stopped taking the pill and desire pregnancy.

There does not appear to be any increase in birth defects in newborn babies when pregnancy occurs soon after stopping the pill.

BIRTH CONTROL AFTER STOPPING THE PILL

If you do not wish to become pregnant after stopping the pill, you should use another method of birth control immediately after stopping Lutera. Speak to your health-care provider about another method of birth control.

OVERDOSAGE

Overdosage may cause nausea, vomiting, breast tenderness, dizziness, abdominal pain and fatigue/drowsiness. Withdrawal bleeding may occur in females. In case of overdosage, contact your health-care provider or pharmacist.

OTHER INFORMATION

Your health-care provider will take a medical and family history before prescribing oral contraceptives and will examine you. The physical examination may be delayed to another time if you request it and your health-care provider believes that it is appropriate to postpone it. You should be reexamined at least once a year. Be sure to inform your health-care provider if there is a family history of any of the conditions listed previously in this leaflet. Be sure to keep all appointments with your health-care provider, because this is a time to determine if there are early signs of side effects of oral-contraceptive use.

Do not use the drug for any condition other than the one for which it was prescribed. This drug has been prescribed specifically for you; do not give it to others who may want birth-control pills.

If you want more information about birth-control pills, ask your health-care provider or pharmacist. They have a more technical leaflet called the Professional Labeling which you may wish to read.

To report SUSPECTED ADVERSE REACTIONS, contact Dr. Reddy’s Laboratories Inc. at 1-888-375-3784 or FDA at 1-800-FDA-1088 or www.fda.gov/medwatch.

Distributed by: Dr. Reddy’s Laboratories Inc.
Princeton, NJ 08540
Product of China

I 0221

Rev. A

Rev. 11/2025